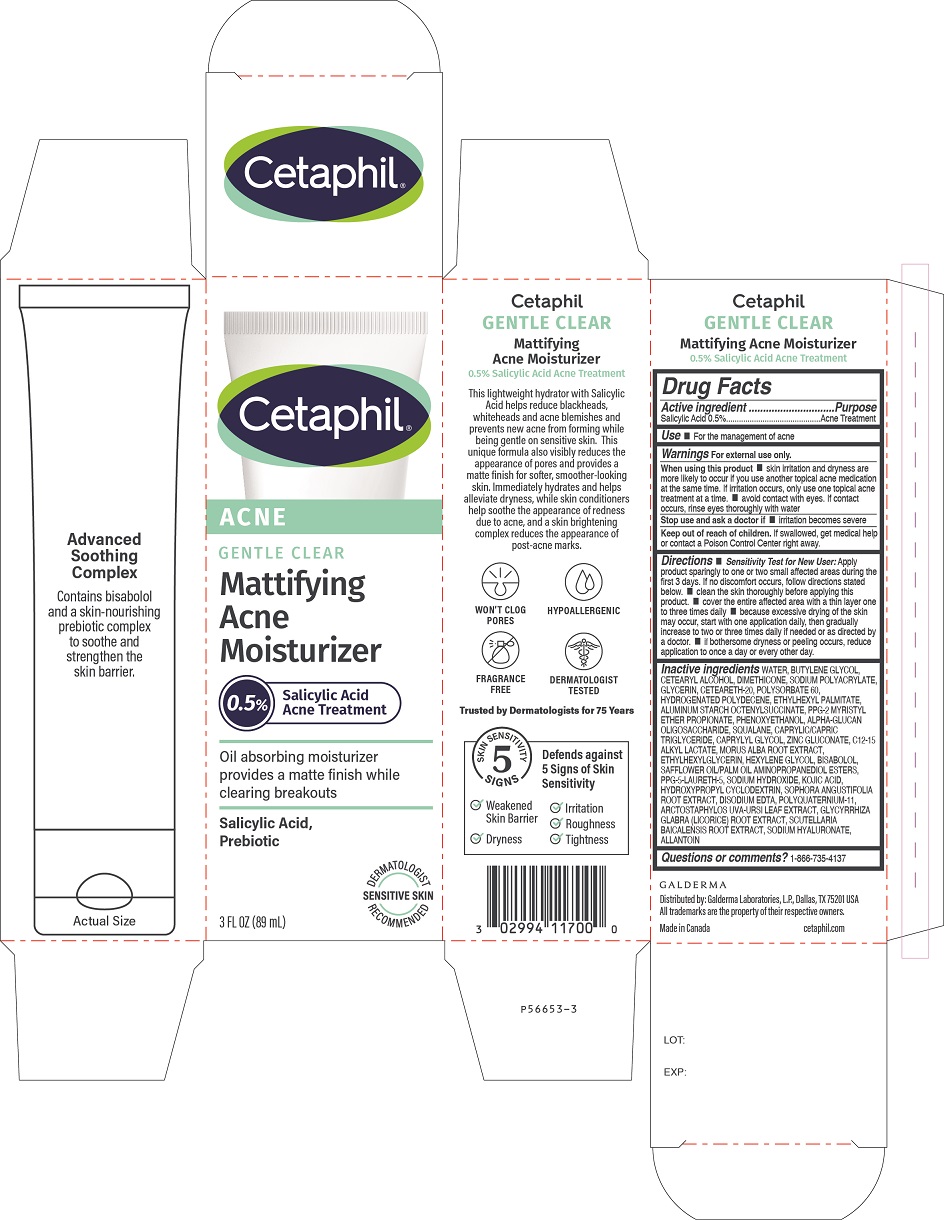 DRUG LABEL: Cetaphil Gentle Clear Mattifying Acne Moisturizer
NDC: 0299-4117 | Form: LOTION
Manufacturer: Galderma Laboratories, L.P.
Category: otc | Type: HUMAN OTC DRUG LABEL
Date: 20241112

ACTIVE INGREDIENTS: Salicylic Acid 5 mg/1 mL
INACTIVE INGREDIENTS: Water; Butylene Glycol; Cetostearyl Alcohol; Dimethicone; Sodium Polyacrylate (2500000 Mw); Glycerin; Polyoxyl 20 Cetostearyl Ether; Polysorbate 60; Hydrogenated Polydecene (550 Mw); Ethylhexyl Palmitate; Aluminum Starch Octenylsuccinate; Ppg-2 Myristyl Ether Propionate; Phenoxyethanol; .Alpha.-Glucan Oligosaccharide; Squalane; Medium-Chain Triglycerides; Caprylyl Glycol; Zinc Gluconate; C12-15 Alkyl Lactate; Morus Alba Root; Ethylhexylglycerin; Hexylene Glycol; Levomenol; Safflower Oil; Ppg-25-Laureth-25; Sodium Hydroxide; Kojic Acid; Hydroxypropyl Betadex; Sophora Flavescens Root; Edetate Disodium; Polyquaternium-11 (1000000 Mw); Arctostaphylos Uva-Ursi Leaf; Glycyrrhiza Glabra; Scutellaria Baicalensis Root; Hyaluronate Sodium; Allantoin

Drug Facts

Active ingredient

Salicylic Acid 0.5%

Purpose
Acne Treatment

Use

● For the management of acne.

Warnings

For external use only.

When using this product • skin irritation and dryness are more likely to occur if you use another topical acne medication at the same time. If irritation occurs, only use one topical acne treatment at a time.• avoid contact with eyes. If contact occurs, rinse eyes thoroughly with water.

Stop use and ask a doctor if ● irritation becomes severe.

Keep out of reach of children.

If swallowed, get medical help or contact a Poison Control Center right away.

Directions

•Sensitivity Test for New User:
Apply product sparingly to one or two small affected areas during the first 3 days. If no discomfort occurs, follow directions stated below. • clean the skin thoroughly before applying this product. • cover the entire affected area with a thin layer one to three times daily • because excessive drying of the skin may occur, start with one application daily, then gradually increase to two or three times daily if needed or as directed by a doctor. • if bothersome dryness or peeling occurs, reduce application to once a day or every other day

Inactive Ingredients

Water, Butylene Glycol, Cetearyl Alcohol, Dimethicone, Sodium Polyacrylate, Glycerin, Ceteareth-20, Polysorbate 60, Hydrogenated Polydecene, Ethylhexyl Palmitate, Aluminum Starch Octenylsuccinate, PPG-2 Myristyl Ether Propionate, Phenoxyethanol, Alpha-Glucan Oligosaccharide, Squalane, Caprylic/Capric Triglyceride, Caprylyl Glycol, Zinc Gluconate, C12-15 Alkyl Lactate, Morus Alba Root Extract, Ethylhexylglycerin, Hexylene Glycol, Bisabolol, Safflower Oil/Palm Oil Aminopropanediol Esters, PPG-5-Laureth-5, Sodium Hydroxide, Kojic Acid, Hydroxypropyl Cyclodextrin, Sophora Angustifolia Root Extract, Disodium EDTA, Polyquaternium-11, Arctostaphylos Uva-Ursi Leaf Extract, Glycyrrhiza Glabra (Licorice) Root Extract, Scutellaria Baicalensis Root Extract, Sodium Hyaluronate, Allantoin

Questions or comments?

1-866-735-4137

Distributed By:
Galderma Laboratories, L.P.
Fort Worth, TX 76177

All trademarks are the property of their respective owners
cetaphil.com

PRINCIPLE DISPLAY PANEL - 3 FL OZ Carton

Cetaphil®

ACNE
GENTLE CLEAR

Mattifying
Acne
Moisturizer

0.5% Salicylic Acid Acne Treatment
Oil Absorbing moisturizer
provides a matte finish while
clearing breakouts
Salicylic Acid,
Prebiotic
Dermatologist Recommended
Sensitive Skin
3 FL OZ (89 mL)

Distributed by: Galderma Laboratories, L.P., Dallas TX 75201 USA
All trademarks are the property of their respective owners.
cetaphil.com
Made in Canada
P56653-3